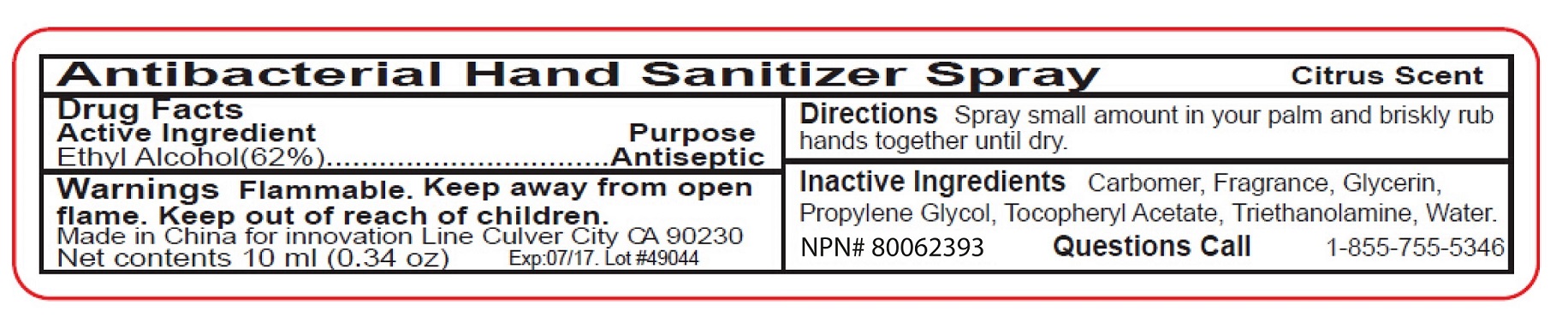 DRUG LABEL: Antibacterial Hand Sanitizer
NDC: 76138-112 | Form: SPRAY
Manufacturer: Innovation Specialties Inc
Category: otc | Type: HUMAN OTC DRUG LABEL
Date: 20240710

ACTIVE INGREDIENTS: ALCOHOL 62 mL/100 mL
INACTIVE INGREDIENTS: CARBOMER HOMOPOLYMER, UNSPECIFIED TYPE; GLYCERIN; PROPYLENE GLYCOL; .ALPHA.-TOCOPHEROL ACETATE; TROLAMINE; WATER

Antibacterial Hand Sanitizer Spray

Active Ingredient

Ethyl Alcohol (62%)

Purpose

Antiseptic

Keep out of reach of children.

Uses

To help clean hands

Warnings

Flammable. Keep away from open flame.

Directions

Spray small amount in your palm and briskly rub hands together until dry.

Inactive Ingredients

Carbomer, Fragrance, Glycerin, Propylene Glycol, Tocopheryl Acetate, Triethanolamine, Water.

Questions

call1-855-755-5346

Made in China for Innovation Line Culver city CA 90230

Citrus Scent